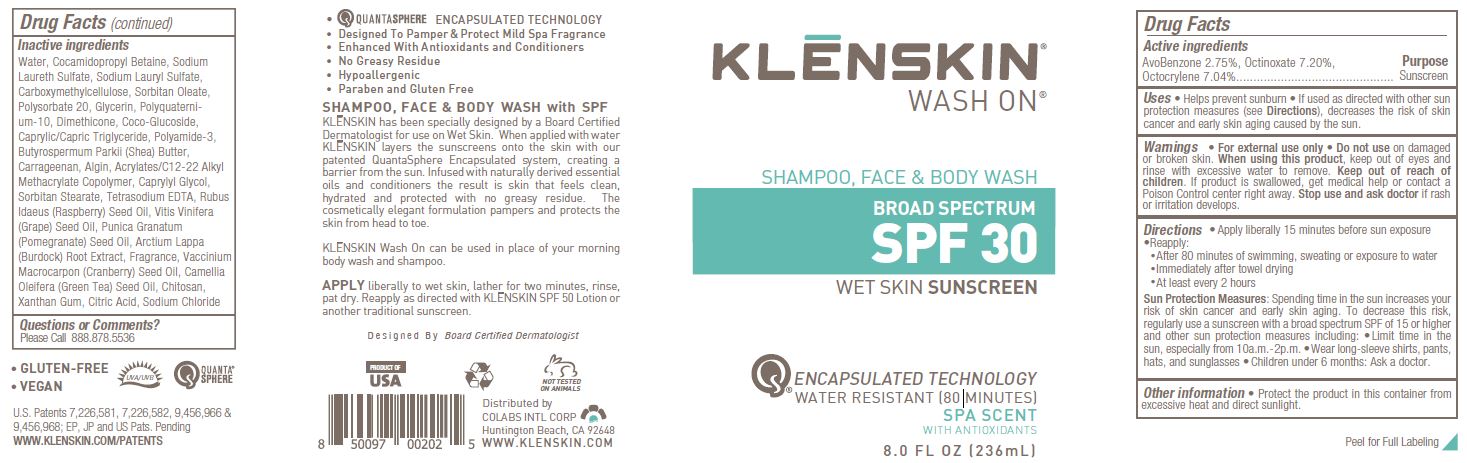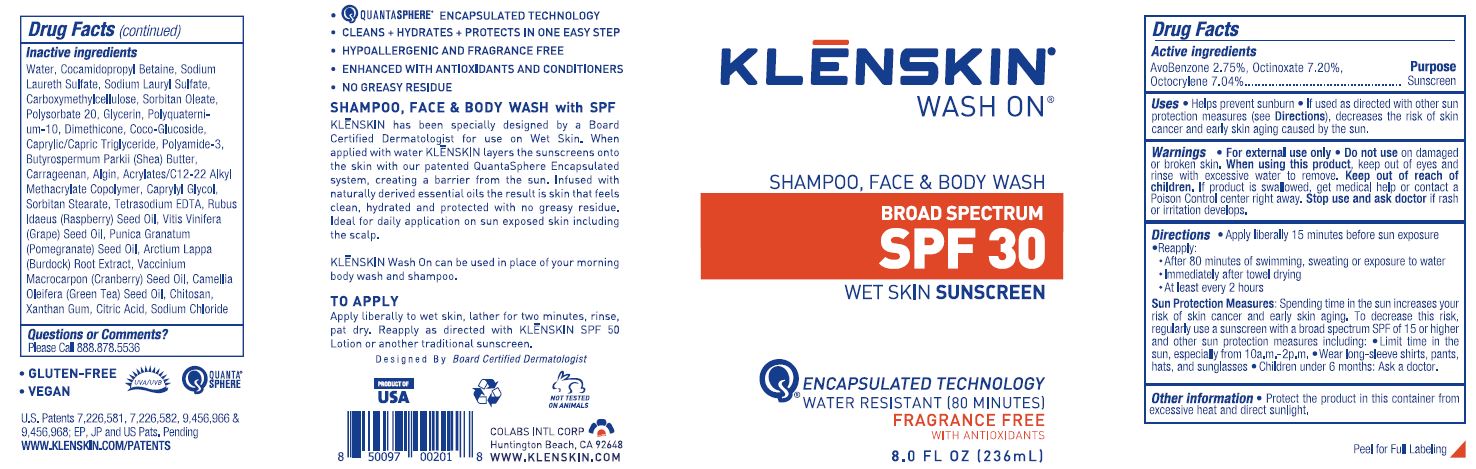 DRUG LABEL: KLENSKIN WASH ON SUNSCREEN
NDC: 61369-106 | Form: GEL
Manufacturer: CoLabs Intl. Corp
Category: otc | Type: HUMAN OTC DRUG LABEL
Date: 20240115

ACTIVE INGREDIENTS: AVOBENZONE 2.75 g/100 mL; OCTOCRYLENE 7.04 g/100 mL; OCTINOXATE 7.2 g/100 mL
INACTIVE INGREDIENTS: WATER; COCAMIDOPROPYL BETAINE; SODIUM LAURETH SULFATE; SODIUM LAURYL SULFATE; CARBOXYMETHYLCELLULOSE; SORBITAN MONOOLEATE; POLYSORBATE 20; GLYCERIN; POLYQUATERNIUM-10 (125 MPA.S AT 2%); DIMETHICONE; COCO GLUCOSIDE; MEDIUM-CHAIN TRIGLYCERIDES; POLYAMIDE-3 (12000 MW); SHEA BUTTER; CARRAGEENAN; SODIUM ALGINATE; BUTYL ACRYLATE/METHYL METHACRYLATE/METHACRYLIC ACID COPOLYMER (18000 MW); CAPRYLYL GLYCOL; SORBITAN MONOSTEARATE; EDETATE SODIUM; RASPBERRY SEED OIL; GRAPE SEED OIL; POMEGRANATE SEED OIL; ARCTIUM LAPPA ROOT; CRANBERRY SEED OIL; CAMELLIA OLEIFERA SEED; CHITOSAN HIGH MOLECULAR WEIGHT (400-800 MPA.S); XANTHAN GUM; ANHYDROUS CITRIC ACID; SODIUM CHLORIDE

COLABS - KLENSKIN WASH ON SPF 30, FRAGRANCE FREE AND SPA SCENT VERSIONS (61369-106)

ACTIVE INGREDIENTS

AVOBENZONE 2.75%

OCTOCRYLENE 7.04%

OCTINOXATE 7.2%

PURPOSE

SUNSCREEN

USES

- HELPS PREVENT SUNBURN
- IF USED AS DIRECTED WITH OTHER SUN PROTECTION MEASURES (SEE DIRECTIONS), DECREASES THE RISK OF SKIN CANCER AND EARLY SKIN AGING CAUSED BY THE SUN.

WARNINGS

- FOR EXTERNAL USE ONLY
- DO NOT USE ON DAMAGED OR BROKEN SKIN.
- WHEN USING THIS PRODUCT, KEEP OUT OF EYES AND RINSE WITH EXCESSIVE WATER TO REMOVE.

Stop use and ask doctor if rash or irritation develops.

KEEP OUT OF REACH OF CHILDREN. IF PRODUCT IS SWALLOWED, GET MEDICAL HELP OR CONTACT A POISON CONTROL CENTER RIGHT AWAY.

DIRECTIONS

- APPLY LIBERALLY 15 MINUTES BEFORE SUN EXPOSURE

- REAPPLY:
- AFTER 80 MINUTES OF SWIMMING, SWEATING OR EXPOSURE TO WATER
- IMMEDIATELY AFTER TOWEL DRYING
- AT LEAST EVERY 2 HOURS

SUN PROTECTION MEASURES: SPENDING TIME IN THE SUN INCREASES YOUR RISK OF SKIN CANCER AND EARLY SKIN AGING. TO DECREASE THIS RISK, REGULARLY USE A SUNSCREEN WITH A BROAD SPECTRUM SPF OF 15 OR HIGHER AND OTHER SUN PROTECTION MEASURES INCLUDING:

- LIMIT TIME IN THE SUN, ESPECIALLY FROM 10 A.M. - 2 P.M.
- WEAR LONG-SLEEVED SHIRTS, PANTS, HATS, AND SUNGLASSES
- CHILDREN UNDER 6 MONTHS: ASK A DOCTOR.

OTHER INFORMATION

- PROTECT THE PRODUCT IN THIS CONTAINER FROM EXCESSIVE HEAT AND DIRECT SUNLIGHT.

INACTIVE INGREDIENTS

SPA SCENT: Water, Cocamidopropyl Betaine, Sodium Laureth Sulfate, Sodium Lauryl Sulfate, Carboxymethylcellulose, Sorbitan Oleate, Polysorbate 20, Glycerin, Polyquaternium-10, Dimethicone, Coco-Glucoside, Caprylic/Capric Triglyceride, Polyamide-3, Butyrospermum Parkii (Shea) Butter, Carrageenan, Algin, Acrylates/C12-22 Alkyl Methacrylate Copolymer, Caprylyl Glycol, Sorbitan Stearate, Tetrasodium EDTA, Rubus Idaeus (Raspberry) Seed Oil, Vitis Vinifera (Grape) Seed Oil, Punica Granatum (Pomegranate) Seed Oil, Arctium Lappa (Burdock) Root Extract, Fragrance, Vaccinium Macrocarpon (Cranberry) Seed Oil, Camellia Oleifera (Green Tea) Seed Oil, Chitosan, Xanthan Gum, Citric Acid, Sodium Chloride

FRAGRANCE FREE: Water, Cocamidopropyl Betaine, Sodium Laureth Sulfate, Sodium Lauryl Sulfate, Carboxymethylcellulose, Sorbitan Oleate, Polysorbate 20, Glycerin, Polyquaternium-10, Dimethicone, Coco-Glucoside, Caprylic/Capric Triglyceride, Polyamide-3, Butyrospermum Parkii (Shea) Butter, Carrageenan, Algin, Acrylates/C12-22 Alkyl Methacrylate Copolymer, Caprylyl Glycol, Sorbitan Stearate, Tetrasodium EDTA, Rubus Idaeus (Raspberry) Seed Oil, Vitis Vinifera (Grape) Seed Oil, Punica Granatum (Pomegranate) Seed Oil, Arctium Lappa (Burdock) Root Extract, Vaccinium Macrocarpon (Cranberry) Seed Oil, Camellia Oleifera (Green Tea) Seed Oil, Chitosan, Xanthan Gum, Citric Acid, Sodium Chloride

QUESTIONS OR COMMENTS?

PLEASE CALL TOLL FREE 888.878.5536